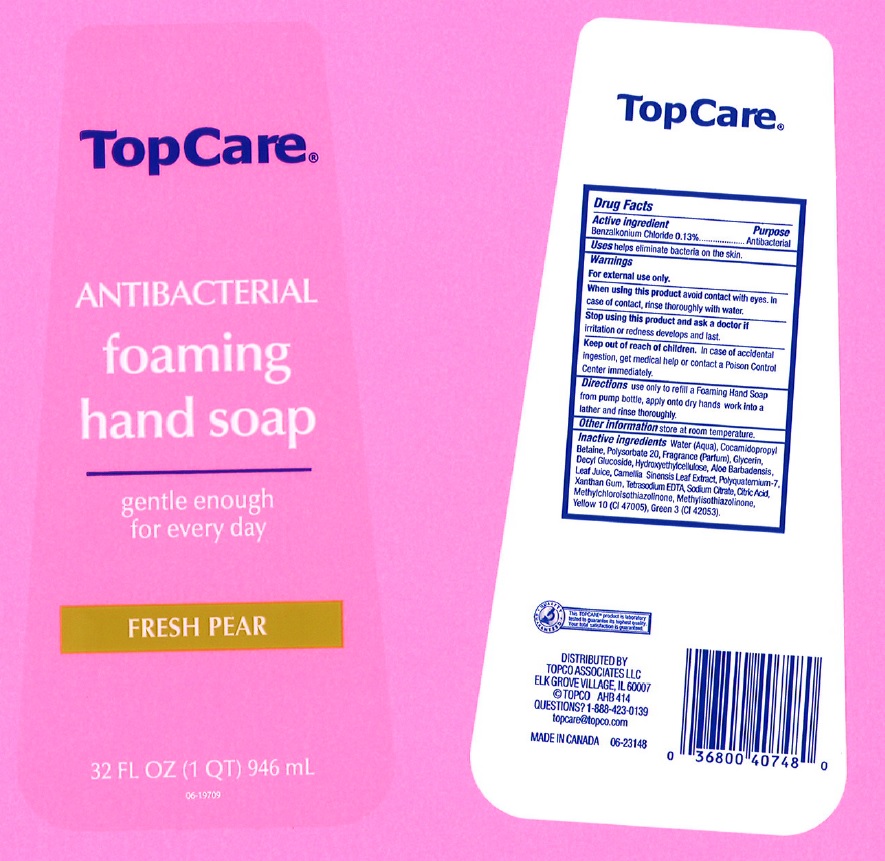 DRUG LABEL: TopCare
NDC: 36800-109 | Form: LIQUID
Manufacturer: TopCo Associates LLC
Category: otc | Type: HUMAN OTC DRUG LABEL
Date: 20170501

ACTIVE INGREDIENTS: BENZALKONIUM CHLORIDE 1.3 mg/1 mL
INACTIVE INGREDIENTS: WATER; COCAMIDOPROPYL BETAINE; POLYSORBATE 20; GLYCERIN; DECYL GLUCOSIDE; HYDROXYETHYL CELLULOSE (5000 CPS AT 1%); ALOE VERA LEAF; GREEN TEA LEAF; POLYQUATERNIUM-7 (70/30 ACRYLAMIDE/DADMAC; 1600000 MW); XANTHAN GUM; EDETATE SODIUM; SODIUM CITRATE; CITRIC ACID MONOHYDRATE; METHYLCHLOROISOTHIAZOLINONE; METHYLISOTHIAZOLINONE; D&C YELLOW NO. 10; FD&C GREEN NO. 3

Drug Facts

Active ingredient

Benzalkonium Chloride 0.13%

Purpose

Antibacterial

Uses

helps eliminate bacteria on the skin.

Warnings

For external use only.

When using this product

avoid contact with eyes. In case of contact, rinse thoroughly with water.

Stop using this product and ask a doctor if

irritation or redness develops and lasts.

Keep out of reach of children.

In case of accidental ingestion, get medical help or contact a Poison Control Cneter immediately.

Directions

Use only to refill a foaming hand soap pump bottle. From pump bottle, apply onto dry hands work into a lather and rinse thoroughly.

Other information

Store at room temperature.

Inactive ingredients

Water (Aqua), Cocamidopropyl Betaine, Polysorbate 20, Fragrance (Parfum), Glycerin, Decyl Glucoside, Hydroxyethylcellulose, Aloe Barbadensis Leaf Juice, Camellia Sinensis Leaf Extract, Polyquaternium-7, Xanthan Gum, Tetrasodium EDTA, Sodium Citrate, Citric Acid, Methylchloroisothiazolinone, Methylisothiazolinone, Yellow 10 (CI 47005), Green 3 (CI 42053).